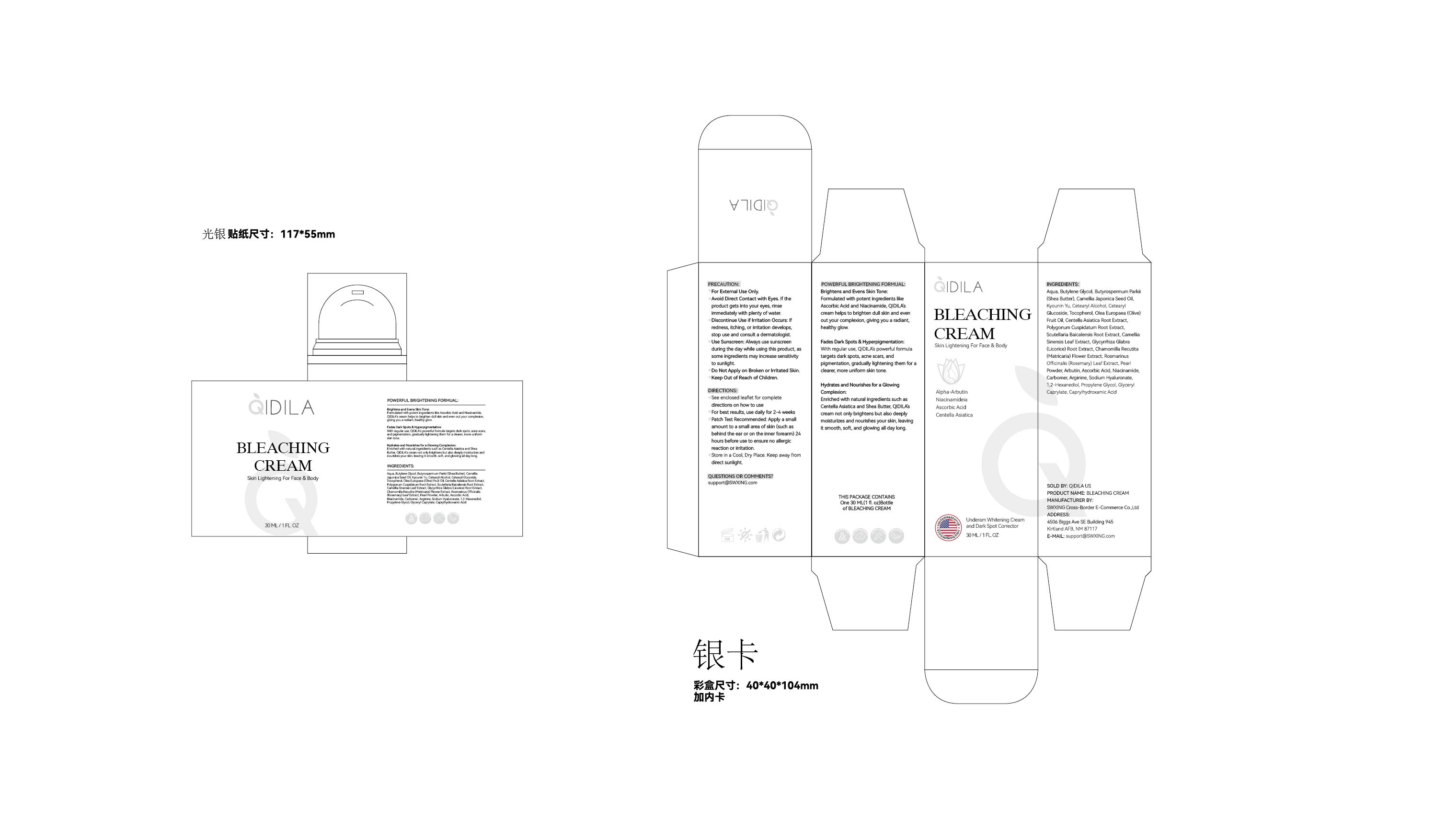 DRUG LABEL: QIDILA Whitening  Skin Lightening Cream
NDC: 85212-0006 | Form: CREAM
Manufacturer: Beijing JUNGE Technology Co., Ltd.
Category: otc | Type: HUMAN OTC DRUG LABEL
Date: 20250218

ACTIVE INGREDIENTS: TOCOPHEROL 1 g/100 mL; BUTYROSPERMUM PARKII (SHEA) BUTTER 3 g/100 mL; PRUNUS ARMENIACA (APRICOT) KERNEL EXTRACT 2 g/100 mL; NIACINAMIDE 0.05 g/100 mL; BUTYLENE GLYCOL 5 g/100 mL; ASCORBIC ACID 0.05 g/100 mL
INACTIVE INGREDIENTS: CENTELLA ASIATICA ROOT 0.5 mL/100 mL; POLYGONUM CUSPIDATUM ROOT 0.5 mL/100 mL; OLEA EUROPAEA (OLIVE) FRUIT OIL 1 mL/100 mL; PROPYLENE GLYCOL 0.02 mL/100 mL; GLYCERYL CAPRYLATE 0.005 mL/100 mL; CAMELLIA JAPONICA SEED OIL 2 mL/100 mL; CARBOMER 0.05 mL/100 mL; CAPRYLHYDROXAMIC ACID 0.0005 mL/100 mL; GLYCYRRHIZA GLABRA (LICORICE) ROOT 0.1 mL/100 mL; SCUTELLARIA BAICALENSIS ROOT 0.2 mL/100 mL; ARBUTIN 0.05 mL/100 mL; MATRICARIA CHAMOMILLA 0.1 mL/100 mL; AQUA 80.4845 mL/100 mL; CAMELLIA SINENSIS LEAF 0.2 mL/100 mL; CETEARYL GLUCOSIDE 1.5 mL/100 mL; CETEARYL ALCOHOL 2 mL/100 mL; 1,2-HEXANEDIOL 0.02 mL/100 mL; ROSEMARY 0.05 mL/100 mL; CALOPHYLLUM INOPHYLLUM SHELL POWDER 0.05 mL/100 mL; ARGININE 0.05 mL/100 mL; SODIUM HYALURONATE 0.02 mL/100 mL

Active Ingredients

BUTYLENE GLYCOL 5%
BUTYROSPERMUM PARKII (SHEA BUTTER) 3%
KYOUNIN YU 2%
TOCOPHEROL 1%
ASCORBIC ACID 0.05%
NIACINAMIDE 0.05%

Purpose

Whitening
Anti-wrinkle
Moisturizing
Nourishing
Anti-aging

Uses

1 .Clean and dry your skin.
2 . Apply a proper amount of the cream on desired area with your fingers, using a circular motion to massage the cream into the skin.
3 .Please apply it twice a day(morning and evening)

Warnings

For external use only. Keep out of reach of children.Avoid contact with eyes.

Keep out of reach of children. If swallowed, get medical help or contact a Poison Control Center right away

CAUTION

After using the product if irritation or rash appears,discontinue use.If irritation or
rash persists.consult your doctor.

DOSAGE

Approximately 0.1oz each time

Inactive Ingredients

AQUA,CAMELLIA JAPONICA SEED OIL,CETEARYL ALCOHOL,CETEARYL GLUCOSIDE,OLEA EUROPAEA (OLIVE) FRUIT OIL,CENTELLA ASIATICA ROOT EXTRACT,POLYGONUM CUSPIDATUM ROOT EXTRACT,SCUTELLARIA BAICALENSIS ROOT EXTRACT,CAMELLIA SINENSIS LEAF EXTRACT,GLYCYRRHIZA GLABRA (LICORICE) ROOT EXTRACT,CHAMOMILLA RECUTITA (MATRICARIA) FLOWER EXTRACT,ROSMARINUS OFFICINALIS (ROSEMARY) LEAF EXTRACT,PEARL POWDER,ARBUTIN,CARBOMER,ARGININE,SODIUM HYALURONATE,1,2-HEXANEDIOL,PROPYLENE GLYCOL,GLYCERYL CAPRYLATE,CAPRYLHYDROXAMIC ACID